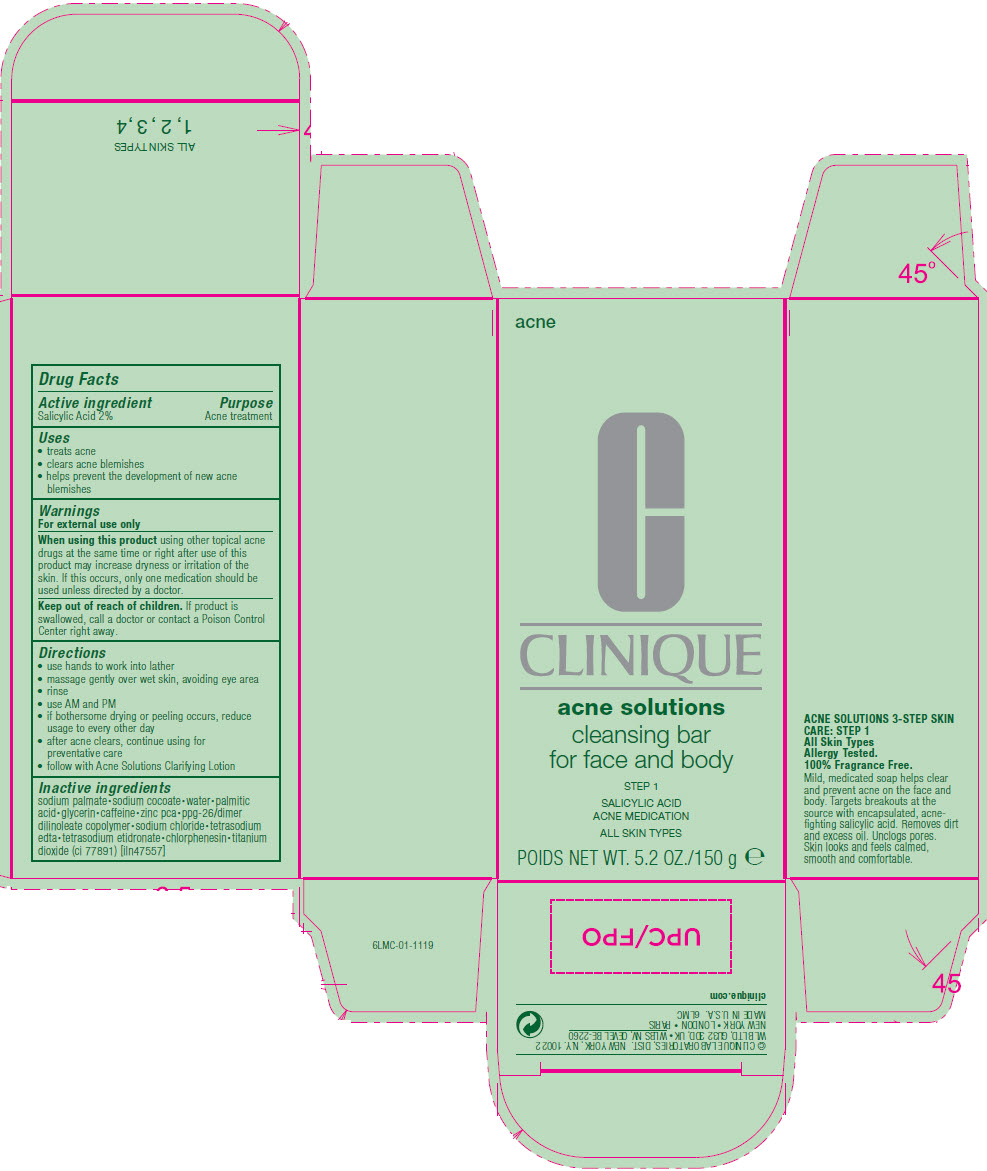 DRUG LABEL: ACNE solutions
NDC: 49527-999 | Form: SOAP
Manufacturer: CLINIQUE LABORATORIES LLC
Category: otc | Type: HUMAN OTC DRUG LABEL
Date: 20230817

ACTIVE INGREDIENTS: SALICYLIC ACID 2 g/100 g
INACTIVE INGREDIENTS: SODIUM PALMATE; SODIUM COCOATE; WATER; PALMITIC ACID; GLYCERIN; CAFFEINE; ZINC PIDOLATE; BIS-PEG-10 DIMETHICONE/DIMER DILINOLEATE COPOLYMER; SODIUM CHLORIDE; EDETATE SODIUM; ETIDRONATE TETRASODIUM; CHLORPHENESIN; TITANIUM DIOXIDE

CLINIQUE
acne solutions

Drug Facts

Active Ingredient

Salicylic Acid 2%

Purpose

Acne treatment

Uses

- treats acne
- clears acne blemishes
- helps prevent the development of new acne blemishes

Warnings

For external use only.

When using this product

using other topical acne drugs at the same time or right after use of this product may increase dryness or irritation of the skin. If this occurs, only one medication should be used unless directed by a doctor.

Keep out of reach of children.

If swallowed, get medical help or contact a Poison Control Center right away.

Directions

- use hands to work into lather
- massage gently over wet skin, avoiding eye area
- rinse
- use AM and PM
- if bothersome drying or peeling occurs, reduce usage to every other day
- after acne clears, continue using for preventative care
- follow with Acne Solutions Clarifying Lotion

Inactive ingredients

sodium palmate∙sodium cocoate∙water∙palmitic acid∙glycerin∙caffeine∙zinc pca∙ppg-26/dimer dilinoleate copolymer∙sodium chloride∙tetrasodium edta∙tetrasodium etidronate∙chlorphenesin∙titanium dioxide (ci 77891) [iln47557]

© CLINIQUE LABORATORIES, DIST.
NEW YORK, N.Y. 10022

PRINCIPAL DISPLAY PANEL - 150 g Carton

acne

CLINIQUE

acne solutions

cleansing bar
for face and body

STEP 1

SALICYLIC ACID
ACNE MEDICATION

ALL SKIN TYPES

NET WT. 5.2 OZ./150 g e